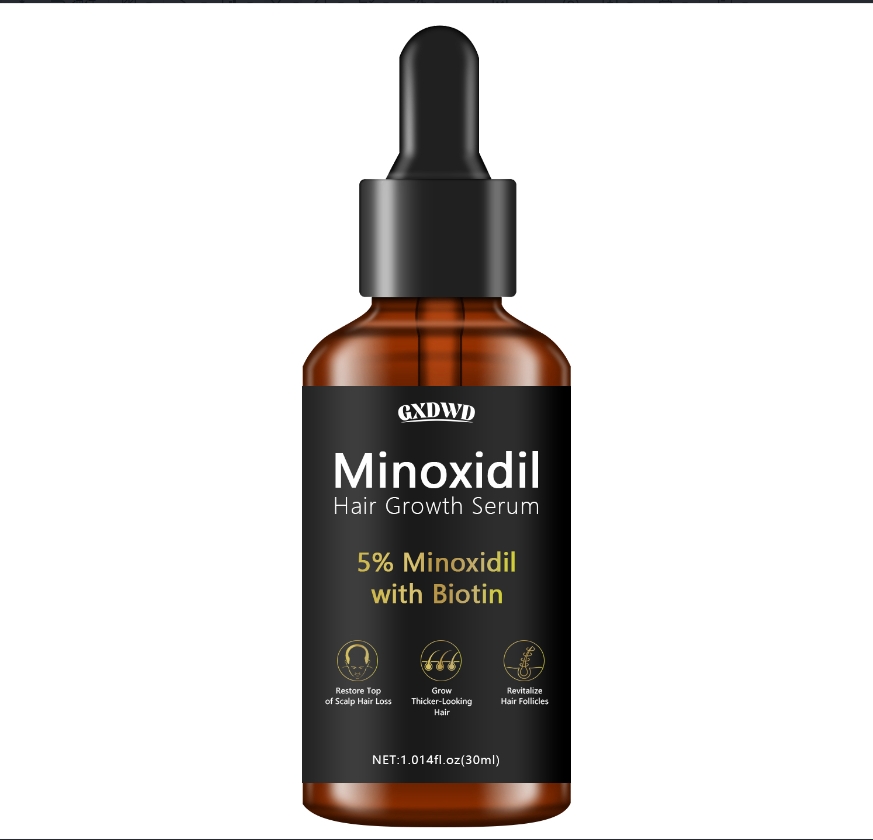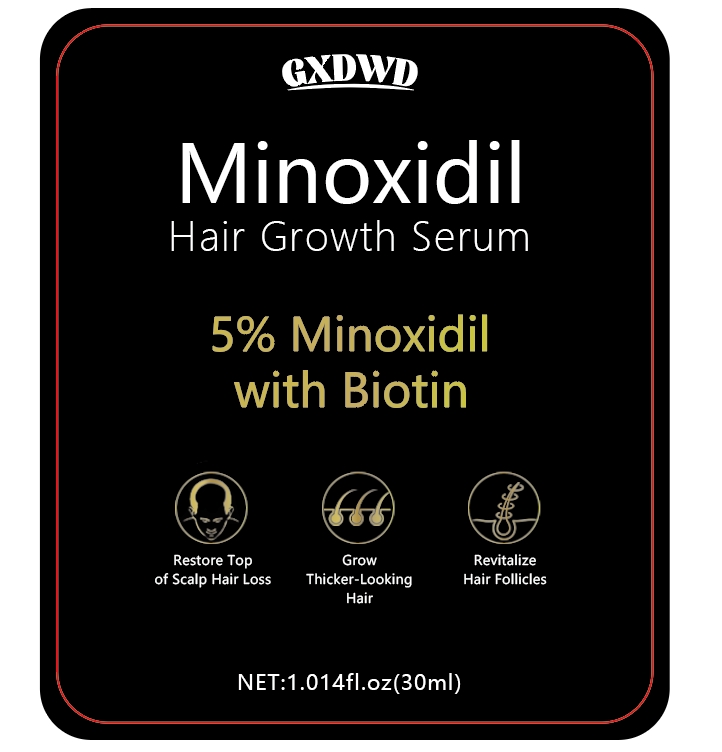 DRUG LABEL: hair care essential oil
NDC: 84025-168 | Form: OIL
Manufacturer: Guangzhou Yanxi Biotechnology Co.. Ltd
Category: otc | Type: HUMAN OTC DRUG LABEL
Date: 20240827

ACTIVE INGREDIENTS: NIACINAMIDE 5 mg/30 mL; CETEARYL OLIVATE 3 mg/30 mL
INACTIVE INGREDIENTS: WATER

DOSAGE AND ADMINISTRATION

Hair care essential oil for nourishing and caring for hair

WARNINGS

keep out of children

INACTIVE INGREDIENT

AQUA

INDICATIONS AND USAGE

For daily hair care

keep out of children

PURPOSE

Effectively relieves dry hair and makes hair smooth